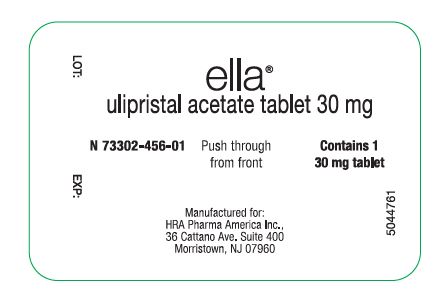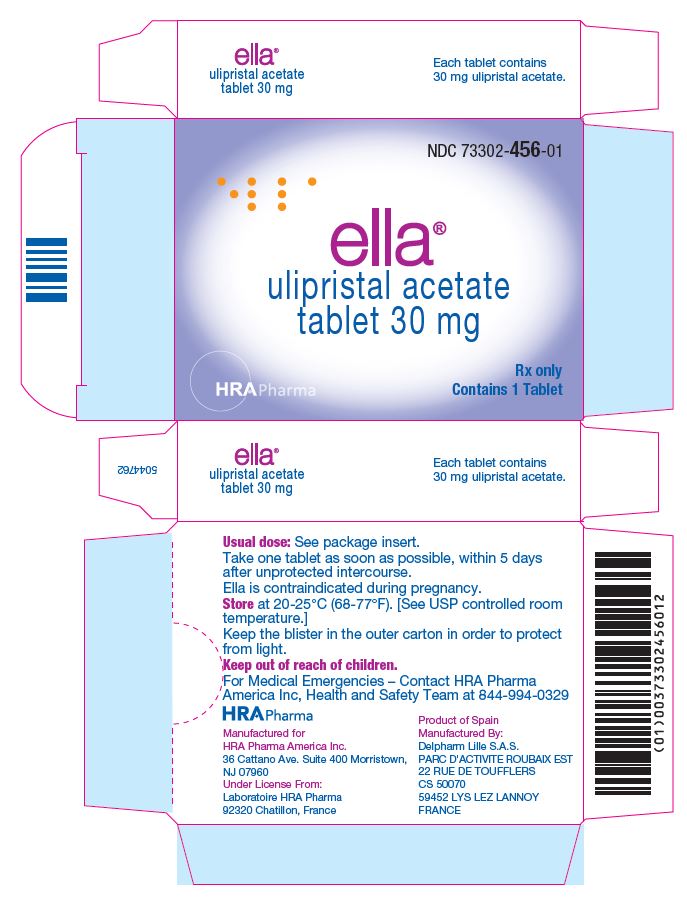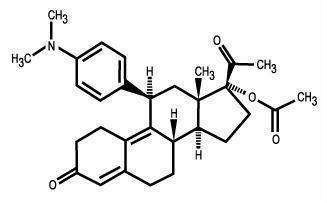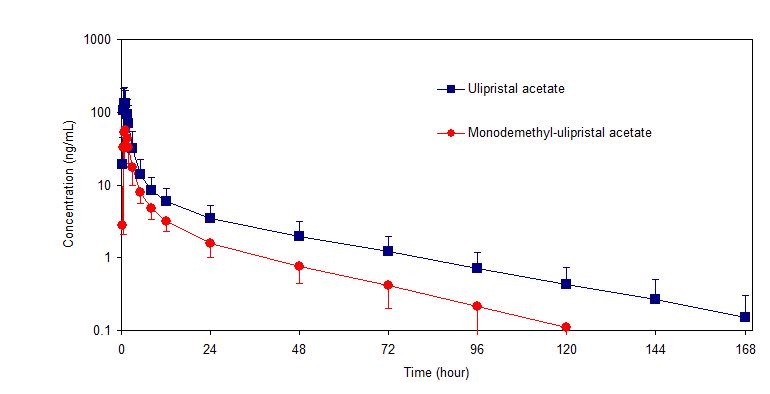 DRUG LABEL: Ella
NDC: 73302-456 | Form: TABLET
Manufacturer: HRA PHARMA AMERICA, INC.
Category: prescription | Type: HUMAN PRESCRIPTION DRUG LABEL
Date: 20260107

ACTIVE INGREDIENTS: ULIPRISTAL ACETATE 30 mg/1 1
INACTIVE INGREDIENTS: LACTOSE MONOHYDRATE; POVIDONE K30; CROSCARMELLOSE SODIUM; MAGNESIUM STEARATE

HIGHLIGHTS OF PRESCRIBING INFORMATION

These highlights do not include all the information needed to use ella safely and effectively. See full prescribing information for ella.
ELLA (ulipristal acetate) tablet, for oral use
Initial U.S. Approval: 2010

RECENT MAJOR CHANGES

- Dosage and Administration (2.1, 2.2, 2.3) | 06/2021
- Warnings and Precautions (5.5) | 06/2021

1 INDICATIONS AND USAGE

Ellais a progesterone agonist/antagonist emergency contraceptive indicated for prevention of pregnancy following unprotected intercourse or a known or suspected contraceptive failure. Ellais not intended for routine use as a contraceptive. (1)

2 DOSAGE AND ADMINISTRATION

- Take one tablet orally as soon as possible, within 120 hours (5 days) after unprotected intercourse or a known or suspected contraceptive failure. Take with or without food. Take at any time during the menstrual cycle. (2.1)
- After ellause, initiate or resume hormonal contraception no sooner than 5 days after the intake of ella and use a reliable barrier method until the next menstrual period. (2.2)
- If vomiting occurs within 3 hours of taking ella, consider repeating the dose. (2.3)

3 DOSAGE FORMS AND STRENGTHS

1. 30 mg tablet (3)

4 CONTRAINDICATIONS

- Known or suspected pregnancy (4)

5 WARNINGS AND PRECAUTIONS

- Existing Pregnancy: ellais not indicated for termination of an existing pregnancy. (5.1)
- Ectopic pregnancy:Evaluate women who become pregnant or complain of lower abdominal pain after taking ellafor ectopic pregnancy. (5.2)
- Fertility Following Use: Rapid return of fertility is likely. Subsequent acts of intercourse should be protected by a reliable barrier method of contraception until the next menstrual period. (5.5)
- Effect on Menstrual Cycle: ellamay alter the next expected menses. If menses is delayed beyond 1 week, rule out pregnancy. (5.6)
- Elladoes not protect against STI/HIV. (5.7)

6 ADVERSE REACTIONS

The most common adverse reactions (≥ 5%) in the clinical trials were headache (18%), abdominal pain (12%), nausea (12%), dysmenorrhea (9%), fatigue (6%) and dizziness (5%). (6)To report SUSPECTED ADVERSE REACTIONS, contact HRA Pharma America Inc., at 844-994-0329 or FDA at 1-800-FDA-1088 or www.fda.gov/medwatch.

7 DRUG INTERACTIONS

- Drugs or herbal products that induce CYP3A4 decrease the effectiveness of ella. (7.1)
- Initiation of progestin-containing contraceptives may impair the ability of ellato delay ovulation. (7.1)

FULL PRESCRIBING INFORMATION

1 INDICATIONS AND USAGE

Ellais a progesterone agonist/antagonist emergency contraceptive indicated for prevention of pregnancy following unprotected intercourse or a known or suspected contraceptive failure [see Dosage and Administration (2.1)] . Ellais not intended for routine use as a contraceptive.

2 DOSAGE AND ADMINISTRATION

2.1 Recommended Dosage and Administration

- Take one tablet of ellaorally as soon as possible within 120 hours (5 days) after unprotected intercourse or a known or suspected contraceptive failure.
- Take ellawith or without food.
- Take ellaat any time during the menstrual cycle.

2.2 Recommendations Regarding Use with Hormonal Contraception

After ellause, initiate or resume hormonal contraception no sooner than 5 days after the intake of ellaand use a reliable barrier method until the next menstrual period. For known or suspected failure of hormonal contraception refer to the hormonal contraceptive’s prescribing information for instructions on what to do [see Warnings and Precautions (5.5), Drug Interactions (7.1)and Clinical Pharmacology (12.2)] .

2.3 Recommendation in Case of Gastrointestinal Disturbances

If vomiting occurs within 3 hours of taking ella, consider repeating the dose.

3 DOSAGE FORMS AND STRENGTHS

The ellatablet is supplied as a white to off-white, round, curved tablet containing 30 mg of ulipristal acetate and is marked " ella" on both sides.

4 CONTRAINDICATIONS

Ellais contraindicated for use in the case of known or suspected pregnancy [see Use in Specific Populations (8.1)].

5 WARNINGS AND PRECAUTIONS

5.1 Existing Pregnancy

Ellais not indicated for termination of an existing pregnancy.

5.2 Ectopic Pregnancy

A history of ectopic pregnancy is not a contraindication to use of this emergency contraceptive method. Healthcare providers, however, should consider the possibility of ectopic pregnancy in women who become pregnant or complain of lower abdominal pain after taking ella. A follow-up physical or pelvic examination is recommended if there is any doubt concerning the general health or pregnancy status of any woman after taking ella.

5.3 Repeated Use

Ellais for occasional use as an emergency contraceptive. It should not replace a regular method of contraception. Repeated use of ellawithin the same menstrual cycle is not recommended, as safety and efficacy of repeat use within the same cycle has not been evaluated.

5.4 CYP3A4 Inducers

A CYP3A4 inducer, rifampin, decreases the plasma concentration of ellasignificantly. Ellashould not be administered with CYP3A4 inducers [see Drug interactions (7.1)and Clinical Pharmacology (12.3)] .

5.5 Fertility Following Use

A rapid return of fertility is likely following treatment with ellafor emergency contraception.

After use of ella, a reliable barrier method of contraception should be used with subsequent acts of intercourse until the next menstrual period.

After using ella, if a woman wishes to initiatehormonal contraception as a regular method, she can do so, no sooner than 5 days after the intake of ellaand she should use a reliable barrier method until the next menstrual period [ see Dosage and Administration (2.2), Drug Interactions (7.1and 7.3) and Clinical Pharmacology (12.2)].

Progestin-containing contraceptives may impair the ability of ellato delay ovulation. Advise women to follow the instructions on the initiation or resumption of hormonal contraceptives after ellaintake [see Dosage and Administration(2.2)].

5.6 Effect on Menstrual Cycle

After ellaintake, menses sometimes occur earlier or later than expected by a few days. In clinical trials, cycle length was increased by a mean of 2.5 days but returned to normal in the subsequent cycle. Seven percent of subjects reported menses occurring more than 7 days earlier than expected, and 19% reported a delay of more than 7 days. If there is a delay in the onset of expected menses beyond 1 week, rule out pregnancy.

Nine percent of women studied reported intermenstrual bleeding after use of ella.

5.7 Sexually Transmitted Infections/HIV

Elladoes not protect against HIV infection (the virus that causes AIDS) or other sexually transmitted infections (STIs).

6 ADVERSE REACTIONS

6.1 Clinical Trials Experience

Because clinical trials are conducted under widely varying conditions, adverse reaction rates observed in the clinical trials of a drug cannot be directly compared to rates in the clinical trials of another drug and may not reflect the rates observed in clinical practice.

Ellawas studied in an open-label multicenter trial (Open-Label Study) and in a comparative, randomized, single-blind, multicenter trial (Single-Blind Comparative Study). In these studies, a total of 2,637 (1,533 + 1,104) women in the 30 mg ulipristal acetate groups were included in the safety analysis. The mean age of women who received ulipristal acetate was 24.5 years and the mean body mass index (BMI) was 25.3. The racial demographics of those enrolled were 67% Caucasian, 20% Black or African American, 2% Asian, and 12% other.

The most common adverse reactions (≥ 10%) in the clinical trials for women receiving ellawere headache (18% overall), nausea (12% overall) and abdominal and upper abdominal pain (12% overall). Table 1lists those adverse reactions that were reported in ≥ 5% of subjects in the clinical studies (14).

Table 1: Adverse Reactions in ≥ 5% of Women (%) Receiving a Single Dose of ella (30 mg Ulipristal Acetate)
Most Common Adverse Reactions | Open-Label Study | Single-Blind Comparative Study
Most Common Adverse Reactions | N = 1,533 | N = 1,104
Headache | 18 | 19
Nausea | 12 | 13
Abdominal and upper abdominal pain | 15 | 8
Dysmenorrhea | 7 | 13
Fatigue | 6 | 6
Dizziness | 5 | 5

6.2 Postmarketing Experience

Adolescents: the safety profile observed in adolescents aged 17 and younger in studies and post-marketing is similar to the safety profile in adults [see Pediatric Use (8.4)] .

The following adverse reactions have been identified during post-approval use of ella:
Skin and Subcutaneous Tissue Disorders: Acne
Hypersensitivity reactions, including rash, urticaria, pruritis, and angioedema

Because these reactions are reported voluntarily from a population of uncertain size, it is not always possible to reliably estimate their frequency or establish a causal relationship to drug exposure.

7 DRUG INTERACTIONS

Several in vivodrug interaction studies have shown that ellais predominantly metabolized by CYP3A4.

7.1 Changes in Emergency Contraceptive Effectiveness Associated with Co-Administration of Other Products

CYP3A inducers

Drugs or herbal products that induce CYP3A4 decrease the plasma concentrations of ella, and may decrease its effectiveness [see Warnings and Precautions (5.4)and Clinical Pharmacology (12.3)] . Avoid co-administration of ellaand drugs or herbal products such as:

- barbiturates
- bosentan
- carbamazepine
- felbamate
- griseofulvin
- oxcarbazepine
- phenytoin
- rifampin
- St. John's Wort
- topiramate

Hormonal contraceptives

Progestin-containing contraceptives may impair the ability of ellato delay ovulation. After using ella, if a woman wishes to initiateor resumehormonal contraception, she can do so, no sooner than 5 days after the intake of ellaand she should use a reliable barrier method until the next menstrual period. If a woman used elladue to a known or suspected failure of her hormonal contraception refer to the hormonal contraceptive’s prescribing information for instructions on what to do [see Dosage and Administration (2.2), Warnings and Precautions (5.5)and Clinical Pharmacology (12.2)] .

7.2 Increase in Plasma Concentrations of ella Associated with Co-Administered Drugs

CYP3A4 inhibitors such as itraconazole or ketoconazole increase plasma concentrations of ella [see Pharmacokinetics (12.3)] .

7.3 Effects of ella on Co-Administered Drugs

Hormonal contraceptives: ellamay impact the effect of the progestin component of hormonal contraceptives. Therefore, if a woman wishes to use hormonal contraception after using ella, she should use a reliable barrier method for subsequent acts of intercourse until her next menstrual period [see Dosage and Administration (2.2), Warnings and Precautions (5.5)and Clinical Pharmacology (12.2)] .

8 USE IN SPECIFIC POPULATIONS

8.1 Pregnancy

Risk Summary

Ellais contraindicated for use during an existing or suspected pregnancy. No signal of concern regarding pregnancy complications was found in postmarketing studies [see Data]. Isolated cases of major malformations in ella-exposed pregnancies were identified; however, the data are not sufficient to determine a risk for birth defects with inadvertent use of elladuring pregnancy. Miscarriage was reported in 14% of the known pregnancy outcomes; a rate that is similar to the U.S. background rate for miscarriage. In the U.S. general population, the estimated background risk of major birth defects and miscarriage in clinically recognized pregnancies is 2-4% and 15-20%, respectively.

In animal reproduction studies, no malformations were observed during repeated administration of ulipristal acetate to pregnant rats, rabbits and monkeys at daily drug exposures ⅓, ½, and 3 times respectively, the human exposure at a dose of 30 mg [ see Data] .

Data

Human Data

Ellapregnancy exposure data was collected in the U.S. and Europe from 1999 to 2015 and analyzed post-marketing using data from interventional clinical trials, observational studies and pharmacovigilance reports. Known pregnancy outcomes were available for 462/784 pregnancies in which women received ellaat doses of 30 mg or greater during the conception cycle or during pregnancy. Data of pregnancies with known outcome were analyzed prospectively for 272 cases and retrospectively for 190 cases. Pregnancy outcomes included 302 elective abortions (2 for fetal anomalies including 1 with trisomy 21), 63 spontaneous abortions, and 13 ectopic pregnancies. No maternal or fetal deaths were reported. 84 pregnancies continued until birth, with congenital anomalies reported in 5 infants, including 4 major malformations (2/4 with genetic syndromes). Although these data do not allow estimation of the prevalence rate of congenital anomalies associated with inadvertent use of ellain pregnancy or determination of a causal relationship between reported anomalies and ella, they show that ella-exposed pregnancies were not associated with a pattern of increased risk of adverse outcomes.

Animal Data

Ulipristal acetate was administered repeatedly to pregnant rats and rabbits during the period of organogenesis. Embryofetal loss was noted in all pregnant rats and in half of the pregnant rabbits following 12 and 13 days of dosing, at daily drug exposures 1/3 and 1/2 the human exposure, respectively, based on body surface area (mg/m^2). There were no malformations of the surviving fetuses in these studies. Adverse effects were not observed in the offspring of pregnant rats administered ulipristal acetate during the period of organogenesis through lactation at drug exposures 1/24 the human exposure based on AUC. Administration of ulipristal acetate to pregnant monkeys for 4 days during the first trimester caused pregnancy termination in 2/5 animals at daily drug exposures 3 times the human exposure based on body surface area.

8.2 Lactation

Risk Summary

Ulipristal acetate and its active metabolite, monodemethyl-ulipristal acetate, are present in human milk in small
amounts (see Data). Based on the levels of drug and active metabolite measured in breastmilk, a fully breastfed child would receive a weight-adjusted dosage of approximately 0.8% of ulipristal acetate and monodemethyl-ulipristal acetate on Day 1 of drug administration and an approximate total of 1% of the maternal dose over a 5-day period after drug administration. There is no information on the effects on the breastfed child or the effects on milk production. The developmental and health benefits of breastfeeding should be considered along with the mother’s clinical need for ellaand any potential adverse effects on the breastfed child from ellaor from the underlying maternal condition.

Data

The breast milk of 12 lactating women following administration of ellawas collected in 24-hour increments to measure the concentrations of ulipristal acetate and the active metabolite monodemethyl-ulipristal acetate in breast milk. The mean daily concentrations of ulipristal acetate in breast milk were 22.7 ng/mL [0-24 hours], 2.96 ng/mL [24-48 hours], 1.56 ng/mL [48-72 hours], 1.04 ng/mL [72-96 hours], and 0.69 ng/mL [96-120 hours]. The mean daily concentrations of monodemethyl-ulipristal acetate in breast milk were 4.49 ng/mL [0-24 hours], 0.62 ng/mL [24-48 hours], 0.28 ng/mL [48-72 hours], 0.17 ng/mL [72-96 hours], and 0.10 ng/mL [96-120 hours]. Using these data, a fully breastfed infant would receive approximately 4.1 mcg/kg of ulipristal acetate and monodemethyl-ulipristal acetate on Day 1 following drug administration and approximately 5.2 mcg/kg over a five day period following drug administration.

8.3 Females and Males of Reproductive Potential

Contraception

Progestin-containing contraceptives may impair the ability of ellato delay ovulation. Advise females to use a reliable barrier method for subsequent acts of intercourse until her next menstrual period.

After using ella, if a woman wishes to initiateor resumehormonal contraception, she can do so, no sooner than 5 days after the intake of ellaand she should use a reliable barrier method of contraception until the next menstrual period. If a woman used elladue to a known or suspected failure of her hormonal contraception refer to the hormonal contraceptive’s prescribing information for instructions on what to do [see Dosage and Administration (2.2), Warnings and Precautions (5.5), Drug Interactions (7), and Clinical Pharmacology (12.2, 12.3)] .

8.4 Pediatric Use

There is no relevant use of ulipristal acetate for children of prepubertal age in the indication emergency contraception .

Adolescents:

Safety and efficacy of ellahave been established in women of reproductive age. The clinical trials of ellaenrolled 41 females under age 18, and a post-marketing observational study evaluating effectiveness and safety of ellain adolescents enrolled 279 females under age 18, including 76 under age 16 years. In these studies, the safety and efficacy profile observed in adolescents aged 17 and younger was similar to that in adults. Use of ellabefore menarche is not indicated.

8.5 Geriatric Use

This product is not intended for use in postmenopausal women.

8.6 Race

While no formal studies have evaluated the effect of race, a cross-study comparison of two pharmacokinetic studies indicated that exposure in South Asians may exceed that in Caucasians and African Americans. However, no difference in efficacy and safety was observed for women of different races in clinical studies.

8.7 Hepatic Impairment

No studies have been conducted to evaluate the effect of hepatic disease on the disposition of ella.

8.8 Renal Impairment

No studies have been conducted to evaluate the effect of renal disease on the disposition of ella.

10 OVERDOSAGE

Experience with ulipristal acetate overdose is limited. In a clinical study, single doses equivalent to up to 4 times ellawere administered to a limited number of subjects without any adverse reactions.

11 DESCRIPTION

The ella(ulipristal acetate) tablet for oral use contains 30 mg of a single active steroid ingredient, ulipristal acetate [17α-acetoxy-11β-(4-N,N-dimethylaminophenyl)-19-norpregna-4,9-diene-3,20-dione], a synthetic progesterone agonist/antagonist. The inactive ingredients are lactose monohydrate, povidone K-30, croscarmellose sodium and magnesium stearate.

Ulipristal acetate is a white to yellow crystalline powder which has a molecular weight of 475.6. The structural formula is:

C30H37NO4

12 CLINICAL PHARMACOLOGY

12.1 Mechanism of Action

When taken immediately before ovulation is to occur, ella postpones follicular rupture. The likely primary mechanism of action of ulipristal acetate for emergency contraception is therefore inhibition or delay of ovulation; however, alterations to the endometrium that may affect implantation may also contribute to efficacy.

12.2 Pharmacodynamics

Ulipristal acetate is a selective progesterone receptor modulator with antagonistic and partial agonistic effects (a progesterone agonist/antagonist) at the progesterone receptor. It binds the human progesterone receptor and prevents progesterone from occupying its receptor.

The pharmacodynamics of ulipristal acetate depend on the timing of administration in the menstrual cycle. Administration in the mid-follicular phase causes inhibition of folliculogenesis and reduction of estradiol concentration.

Pharmacodynamic data showed that administration of ellato 34 women in the late follicular phase postponed follicular rupture for at least 5 days in all (100%) of 8 subjects who took ellabefore the luteinizing hormone (LH) surge and 11 (79%) of 14 subjects who took ellaimmediately before ovulation (when LH has already started to rise). However, treatment was not effective in postponing follicular rupture when administered on the day of LH peak.

Dosing in the early luteal phase does not significantly delay endometrial maturation but decreases endometrial thickness by 0.6 ± 2.2 mm (mean ± SD).

Hormonal Contraceptives after ella intake:

In women initiating hormonal contraception (quickstart scenario):

When a combined oral contraceptive pill (COC) containing ethinyl estradiol 30 µg + levonorgestrel 150 µg was started the day after ellaintake during the follicular phase, elladid not interfere with the COC’s ability to suppress ovarian activity, as assessed by measurement of follicle size via transvaginal ultrasound, combined with serum progesterone and estradiol levels: ovarian activity was suppressed in 61.5% (24/39) of subjects receiving ellaplus COC and 62.2% (23/37) of subjects receiving a placebo plus the COC. The incidence of ovulation was similar between the group that received ellaplus the COC [33.3% (13/39)] and the group that received a placebo plus the COC [32.4% (12/37)]. [see Dosage and Administration (2.2), Warnings and Precautions (5.5)and Drug Interactions (7.3)] .

The initiation of a desogestrel 75 µg progestin-only pill (POP) the day after ellaintake during the follicular phase was associated with a higher incidence of ovulation in the six days following ellaintake compared to an ella-only treatment group, and a relatively slower onset (3 to 4 days) of thickened cervical mucus compared to a group given desogestrel without prior ellaintake (2 days), suggesting an effect of prior use of ellaon the ability of desogestrel to inhibit mucus permeability. [See Dosage and Administration (2.2), Warnings and Precautions (5.5)and Drug Interactions (7.1; 7.3)] .

When a COC containing ethinyl estradiol 30 µg + levonorgestrel 150 µg was started 2 days after ellaintake, ella's ability to delay ovulation, as assessed by transvaginal ultrasound, was reduced: follicular rupture occurred in 9/33 subjects (27%) in less than 5 days, compared to 1/33 subjects after ellaalone (3%). [See Dosage and Administration (2.2), Warnings and Precautions (5.5)and Drug Interactions (7.1)] .

In women resuming combined hormonal contraception (missed pills scenario):

The effects on ovarian activity of delaying versus immediately resuming COCs after ellaintake were investigated in 49 women who had been using COCs containing ethinyl estradiol 30 µg + levonorgestrel 150 µg once daily for 21 days followed by 7 days of placebo pills for at least one cycle. All subjects missed three consecutive pills (Days 5-7) during the first week of pills in the subsequent cycle and took ellaon the following day (Day 8). These subjects were randomized to resume their COCs either on the same day as ellaintake versus five days later. No ovulations with potential risk of pregnancy occurred in either group in the five days following ellaintake. However, in the group that waited five days to resume taking COCs, 4/23 (17.4%) women did ovulate later in the cycle (Days 18-26) whereas no ovulations (0/26) occurred in the group that resumed COC intake on the same day as ella intake. Whether similar results can be expected with other COC products containing different progestins or missed active pills during different weeks in a treatment cycle is unknown.

12.3 Pharmacokinetics

Absorption

Following a single dose administration of ellain 20 women under fasting conditions, maximum plasma concentrations of ulipristal acetate and the active metabolite, monodemethyl-ulipristal acetate, were 176 and 69 ng/ml and were reached at 0.9 and 1 hour, respectively.

Figure 1: Mean (± SD) Plasma Concentration-time Profile of Ulipristal Acetate and Monodemethyl-ulipristal Acetate Following Single Dose Administration of 30 mg Ulipristal Acetate

Table 2: Pharmacokinetic Parameter Values Following Administration of ella (ulipristal acetate) Tablet 30 mg to 20 Healthy Female Volunteers under Fasting Conditions
 | Mean (± SD)
 | Cmax (ng/ml) | AUC0-t (ng•hr/ml) | AUC0-∞ (ng•hr/ml) | tmax (hr)* | t1/2 (hr)
Ulipristal acetate | 176 (89) | 548 (259) | 556 (260) | 0.9 (0.5-2.0) | 32 (6.3)
Monodemethyl- ulipristal acetate | 69 (26) | 240 (59) | 246 (59) | 0.9 (0.8-2.0) | 27 (6.9)

Cmax= maximum concentration
AUC0-t= area under the drug concentration curve from time 0 to time of last determinable concentration
AUC0-∞= area under the drug concentration curve from time 0 to infinity
tmax= time to maximum concentration
t1/2= elimination half-life
* Median (range)

Effect of food: Administration of ellatogether with a high-fat breakfast resulted in approximately 40 - 45% lower mean Cmax, a delayed tmax(from a median of 0.75 hours to 3 hours) and 20 - 25% higher mean AUC0-∞of ulipristal acetate and monodemethyl-ulipristal acetate compared with administration in the fasting state. These differences are not expected to impair the efficacy or safety of ellato a clinically significant extent; therefore, ellacan be taken with or without food.

Distribution

Ulipristal acetate is highly bound (> 94%) to plasma proteins, including high density lipoprotein, alpha-l-acid glycoprotein, and albumin.

Metabolism

Ulipristal acetate is metabolized to mono-demethylated and di-demethylated metabolites. In vitrodata indicate that this is predominantly mediated by CYP3A4. The mono-demethylated metabolite is pharmacologically active.

Excretion

The terminal half-life of ulipristal acetate in plasma following a single 30 mg dose is estimated to be 32.4 ± 6.3 hours.

Drug interactions

CYP3A4 inducers:When a single 30 mg dose of ulipristal acetate was administered following administration of the strong CYP3A4 inducer, rifampin 600 mg once daily for 9 days, Cmaxand AUC of ulipristal acetate decreased by 90% and 93% respectively. The Cmaxand AUC of monodemethyl-ulipristal acetate decreased by 84% and 90% respectively [see Drug Interactions (7.1)] .

CYP3A4 inhibitors:When a single 10 mg dose of ulipristal acetate was administered following administration of the strong CYP3A4 inhibitor, ketoconazole 400 mg once daily for 7 days, Cmaxand AUC of ulipristal acetate increased by 2- and 5.9- fold, respectively. While the AUC of monodemethyl-ulipristal acetate increased by 2.4-fold, Cmaxof monodemethyl-ulipristal acetate decreased by 47%. There was no in vivodrug-drug interaction study between ulipristal acetate 30 mg and CYP3A4 inhibitors [see Drug Interactions (7.1)] .

In vitrostudies demonstrated that elladoes not induce or inhibit the activity of cytochrome P450 enzymes.

P-glycoprotein (P-gp)transporter: In vitrodata indicate that ulipristal may be an inhibitor of P-gp at clinically relevant concentrations. When a single 60 mg dose of fexofenadine, a substrate of P-gp glycoprotein, was administered 1.5 hours after the administration of a single 10 mg dose of ulipristal acetate, there was no increase in Cmaxor AUC of fexofenadine.

Breast Cancer Resistance Protein (BCRP)transporter: In vitrodata indicate that ulipristal acetate may be an inhibitor of BCRP at the intestinal level.

The effects of ellaon P-gp and BCRP transporters are unlikely to have any clinical consequences when considering ella's single dose treatment regimen, although there was no in vivodrug interaction study between ulipristal acetate 30 mg (ella) and substrates of P-pg and BCRP transporters.

13 NONCLINICAL TOXICOLOGY

13.1 Carcinogenesis, Mutagenesis, Impairment of Fertility

Carcinogenicity:

Carcinogenicity potential was evaluated in rats and mice.

Sprague Dawley rats were exposed to ulipristal acetate daily for 99-100 weeks at doses of 1, 3, or 10 mg/kg/day, representing exposures up to 31 times higher than exposures at the maximum recommended human dose (MRHD). There were no drug-related neoplasms in male rats. In female rats, potential treatment-related neoplastic findings were limited to adrenal cortical adenomas in the intermediate dose group (3 mg/kg/day). Despite the increase, this incidence of adrenal cortical adenomas in females may not be relevant to clinical use.

Tg.rasH2 transgenic mice were exposed to ulipristal acetate for 26 weeks at doses of 5, 45, or 130 mg/kg/day, representing exposures 100 times higher than exposures at the MRHD. There was no drug-related increase in neoplasm incidence in male or female mice.

Genotoxicity: Ulipristal acetate was not genotoxic in the Ames assay, in vitromammalian assays utilizing mouse lymphoma cells and human peripheral blood lymphocytes , and in an in vivomicronucleus assay in mice.

Impairment of Fertility: Single oral doses of ulipristal acetate prevented ovulation in 50% of rats at 2 times the human exposure based on body surface area (mg/m^2). Single doses of ulipristal acetate given on post-coital days 4 or 5 prevented pregnancy in 80-100% of rats and in 50% of rabbits when given on post-coital days 5 or 6 at drug exposures 4 and 12 times the human exposure based on body surface area. Lower doses administered for 4 days to rats and rabbits were also effective at preventing ovulation and pregnancy .

14 CLINICAL STUDIES

Two multicenter clinical studies evaluated the efficacy and safety of ella. An open-label study provided the primary data to support the efficacy and safety of ulipristal acetate for emergency contraception when taken 48 to 120 hours after unprotected intercourse. A single-blind comparative study provided the primary data to support the efficacy and safety of ulipristal acetate for emergency contraception when taken 0 to 72 hours after unprotected intercourse and provided supportive data for ulipristal acetate for emergency contraception when taken > 72 to 120 hours after unprotected intercourse. Women in both studies were required to have a negative pregnancy test prior to receiving emergency contraception. The primary efficacy analyses were performed on subjects less than 36 years of age who had a known pregnancy status after taking study medication.

Table 3: Summary of Clinical Trial Results for Women Who Received a Single Dose of ella (30 mg Ulipristal Acetate)
 | Open-Label Study 48 to 120 Hours * | Single-Blind Comparative Study 0 to 72 Hours *
 | N = 1,242 | N = 844
Expected Pregnancy Rate ** | 5.5 | 5.6
Observed Pregnancy Rate ** (95% confidence interval) | 2.2 (1.5, 3.2) | 1.9 (1.1, 3.1)

* Time after unprotected intercourse when ellawas taken
** Number of pregnancies per 100 women at risk for pregnancy

14.1 Open-Label Study

This study was a multicenter open-label trial conducted at 40 family planning clinics in the United States. Healthy women with a mean age of 24 years who requested emergency contraception 48 to 120 hours after unprotected intercourse received a dose of 30 mg ulipristal acetate (ella). The median BMI for the study subjects was 25.3 and ranged from 16.1 to 61.3 kg/m^2.

Twenty-seven pregnancies occurred in 1,242 women aged 18 to 35 years evaluated for efficacy. The number of pregnancies expected without emergency contraception was calculated based on the timing of intercourse with regard to each woman’s menstrual cycle. Ellastatistically significantly reduced the pregnancy rate, from an expected rate of 5.5% to an observed rate of 2.2%, when taken 48 to 120 hours after unprotected intercourse.

14.2 Single-Blind Comparative Study

This study was a multicenter, single-blind, randomized comparison of the efficacy and safety of 30 mg ulipristal acetate (ella) to levonorgestrel (another form of emergency contraception). Subjects were enrolled at 35 sites in the U.S., the United Kingdom and Ireland, with the majority (66%) having been enrolled in the U.S. Healthy women with a mean age of 25 years who requested emergency contraception within 120 hours of unprotected intercourse were enrolled and randomly allocated to receive ellaor levonorgestrel 1.5 mg. The median BMI for the study subjects was 25.3 and ranged from 14.9 to 70.0 kg/m^2.

In the ellagroup, 16 pregnancies occurred in 844 women aged 16 to 35 years when emergency contraception was taken 0 to 72 hours after unprotected intercourse. The number of pregnancies expected without emergency contraception was calculated based on the timing of intercourse with regard to each woman's menstrual cycle; ellastatistically significantly reduced the pregnancy rate, from an expected 5.6% to an observed 1.9%, when taken within 72 hours after unprotected intercourse. There were no pregnancies observed in the women who were administered ellamore than 72 hours after unprotected intercourse (10% of women who received ella).

14.3 Pooled Analysis

Data from the two studies were pooled to provide a total efficacy population of women treated with ulipristal acetate up to 120 hours after unprotected intercourse. Time Trend analysis for the five 24-hour intervals from 0 to 120 hours between unprotected intercourse and treatment was conducted. There were no significant differences in the observed pregnancy rates across the five time intervals.

Subgroup analysis of the pooled data by BMI showed that for women with BMI > 30 kg/m^2 (16% of all subjects), the observed pregnancy rate was 3.1% (95% CI: 1.7, 5.7), which was not significantly reduced compared to the expected pregnancy rate of 4.5% in the absence of emergency contraception taken within 120 hours after unprotected intercourse. In the comparative study, a similar effect was seen for the comparator emergency contraception drug, levonorgestrel 1.5 mg. For levonorgestrel, when used by women with BMI > 30 kg/m^2, the observed pregnancy rate was 7.4% (95% CI: 3.9, 13.4), compared to the expected pregnancy rate of 4.4% in the absence of emergency contraception taken within 72 hours after unprotected intercourse.

16 HOW SUPPLIED/STORAGE AND HANDLING

Ella(ulipristal acetate) tablet, 30 mg is supplied in a PVC-PE-PVDC or PVC-PVDC-aluminum blister. The tablet is a white to off-white, round, curved tablet marked with “ ella” on both sides.

NDC 73302-456-01 (1 tablet unit of use package)

Store at 20-25°C (68-77°F); excursions permitted to 15-30°C (59-86°F) [See USP controlled room temperature.]

Keep the blister in the outer carton in order to protect from light. Keep out of reach of children.

17 PATIENT COUNSELING INFORMATION

Advise the patient to read the FDA-Approved patient Labeling (Patient Information).

Administration Instructions

- Instruct patients to take ellaas soon as possible and not more than 120 hours after unprotected intercourse or a known or suspected contraceptive failure.
- Advise patients to contact their healthcare provider immediately in case of vomiting within 3 hours of taking the tablet, to discuss whether to take another tablet.
- Advise patients that after using ella, a reliable barrier method of contraception should be used for all subsequent acts of intercourse until the next menstrual period.
- Advise patients that after using ella, additional levonorgestrel emergency contraceptive pills should not be used within 5 days of ellaintake.
- Advise patients that after using ella, hormonal contraception should be initiated or resumed no sooner than 5 days after the intake of ellaand to use a reliable contraceptive barrier method until the next menstrual period.
- Advise patients with known or suspected failure of a hormonal contraceptive to refer to the hormonal contraceptive’s prescribing information for instructions on what to do.

Ectopic Pregnancy
Advise patients to seek medical attention if they experience severe lower abdominal pain 3 to 5 weeks after taking ella, in order to be evaluated for an ectopic pregnancy [see Warnings and Precautions (5.2)] .

Effect on Menstrual Cycle
Advise women that after ellaintake, menses may occur earlier or later than expected, by a few days. Advise patients to contact their healthcare provider and consider the possibility of pregnancy if their period is delayed after taking ellaby more than 1 week beyond the date it was expected [see Warnings and Precautions (5.6)] .

Sexually Transmistted Infections/HIV
Inform women that elladoes not protect against HIV infection (the virus that causes AIDS) and other sexually transmitted diseases/infections [see Warnings and Precautions (5.7)].

Drug Interactions
Advise women to inform their healthcare provider if they take herbal supplements such as St. John’s wort [see Drug Interactions (7.1)].

Patient Information
ella(el-uh)
(ulipristal acetate)
tablet, for oral use
Read this Patient Information Leaflet before you take ella. There may be new information. This information does not take the place of talking to your healthcare provider about your medical condition or treatment.
What is ella?
● | Ellais a prescription emergency contraceptive that reduces your chance of becoming pregnant if your birth control fails or you have unprotected sex.
● | Ellashould not be used as your regular birth control. It is very important that you have a reliable form of birth control that is right for you.
● | Ellawill not protect you against HIV infection (the virus that causes AIDS) and other sexually transmitted infections (STIs).
Who should not take ella?
Do not take ellaif:
● | you know or suspect you are already pregnant. Ellais not for use to end an existing pregnancy.
What should I tell my healthcare provider before taking ella? Before you take ella, tell your healthcare provider about all of your medical conditions, including if you:
● | have a history of pregnancy outside the womb, usually in a fallopian tube (ectopic pregnancy).
● | have taken elladuring the same menstrual cycle for a different act of unprotected sex or birth control failure. Do nottake ellamore than 1 time in the same menstrual cycle.
● | are breastfeeding or plan to breastfeed. A small of amount of the hormones in ellamay pass into your breast milk. Talk to healthcare provider about the best birth control for you while breastfeeding.
Tell your healthcare provider about all the medicines you take, including prescription and over-the counter medicines, vitamins, and herbal supplements.
Using some other medicines may make ellaless effective. Especially tell your healthcare provider if you take: a hormonal form of birth control such as birth control pills, implant, IUD (intrauterine device) or patch, St. John’s Wort, bosentan, griseofulvin, phenytoin, topiramate, oxcarbazepine, carbamazepine, barbiturates, rifampin, and felbamate. Know the medicines you take. Keep a list of them to show your healthcare provider and pharmacist when you get a new medicine.
How does ella work?
Ellais thought to work for emergency contraception primarily by stopping or delaying the release of an egg from the ovary. It is possible that ellamay also work by preventing attachment (implantation) to the uterus.
How should I take ella?
● | Take ellaas soon as possible within 5 days (120 hours) after unprotected sex or if you had a birth control failure.
● | Ellacan be taken with or without food.
● | Contact your healthcare provider right away if you vomit within 3 hours of taking ella. Your healthcare provider may prescribe another dose of ellafor you.
● | Ellacan be taken at any time during the menstrual cycle.
● | Ellais meant for emergency contraception only and is not to be used frequently or as a regular birth control. If you need to use emergency contraception often, talk to your healthcare provider and learn about methods of birth control that are right for you and about sexually transmitted infection prevention.
● | After using ella, you should use a reliable barrier birth control method (such as condom with spermicide) each time you have sex until your next menstrual period.
● | After using ella, do notuse any additional levonorgestrel emergency contraceptive pills within 5 days after taking ella.
● | After using ella, wait 5 days to startor resumehormonal birth control as a regular method (such as the pill, patch or vaginal ring). If you used ellabecause you had a problem with your hormonal birth control, follow the instructions provided for that specific hormonal birth control product or contact your healthcare provider for further information. Be sure to use a reliable barrier birth control method (such as a condom with spermicide) each time you have sex until your next menstrual period.
What are the possible side effects of ella?
● | Pregnancy outside of the womb (ectopic pregnancy).If you have severe lower stomach (abdominal) pain about 3 to 5 weeks after taking ella,you may have a pregnancy outside of the uterus (womb), which is called an ectopic or tubal pregnancy. An ectopic pregnancy is a serious condition that needs medical treatment right away. Call your healthcare provider or go to the nearest emergency room right away if you think you may have an ectopic pregnancy.
● | Changes in menstrual cycle.Some women taking ellamay have their next period earlier or later than expected. If your period is more than a week late, you should take a pregnancy test and follow up with your healthcare provider.
The most common side effects of ellainclude:
○ headache
○ nausea
○ stomach (abdominal) pain
○ menstrual pain (dysmenorrhea)
○ tiredness
○ dizziness
Tell your healthcare provider if you have any side effect that bothers you or that does not go away. These are not all the possible side effects of ella. For more information, ask your healthcare provider or pharmacist.
Call your doctor for medical advice about side effects. You may report side effects to FDA 1-800-FDA-1088.
How should I store ella?
● | Store ellaat room temperature between 68°F to 77°F (20°C to 25°C).
● | Protect ellafrom light. Keep ellain the blister card inside the original box until you are ready to take it.
Keep ellaand all medicines out of the reach of children.
General information about the safe and effective use of ella:
Medicines are sometimes prescribed for purposes other than those listed in a Patient Information Leaflet. Do not use ellafor a condition for which it was not prescribed. Do not give ellato other people, even if they have the same symptoms that you have. It may harm them.
This Patient Information Leaflet summarizes the most important information about ella. If you would like more information, talk with your healthcare provider. You can ask your pharmacist or healthcare provider for information about ellathat is written for health professionals.
What are the ingredients in ella?
Active ingredients: ulipristal acetate, 30 mg
Inactive ingredients: lactose monohydrate, povidone, croscarmellose sodium, and magnesium stearate
Manufactured for:
HRA Pharma America Inc.
Morristown, NJ 07960
Under License From:
Laboratoire HRA Pharma
92320 Chatillon, France
ella®is a registered trademark of Laboratoire HRA Pharma
Manufactured by:
Cenexi, 95520 Osny, France, or
Laboratorios León Farma S.A., 24008 León, Spain or
Delpharm Lille SAS, 59452 Lys-Lez-Lannoy, France
For more information, go to www.ella-now.com or call 844-994-0329.
This Patient Information has been approved by the U.S. Food and Drug Administration
Revised: June 2021

General information about the safe and effective use of ella:

PRINCIPAL DISPLAY PANEL - 30 mg Tablet Blister Pack Carton

NDC 73302- 456-01
ella®
ulipristal acetate
tablet 30 mg
HRAPharma
Rx only
Contains 1 Tablet
ella®
ulipristal acetate
tablet 30 mg
Each tablet contains
30 mg ulipristal acetate.
Usual dose:See package insert.
Take one tablet as soon as possible, within 5 days after unprotected intercourse.
Ella is contraindicated during pregnancy.
Storeat 20-25°C (68-77°F). [See USP controlled room temperature.]
Keep the blister in the outer carton in order to protect from light.
Keep out of reach of children.
For Medical Emergencies - Contact HRA Pharma America Inc, Health and Safety Team at 844-994-0329
HRAPharma
Manufactured for
HRA Pharma America Inc.
36 Cattano Ave. Suite 400 Morristown,
NJ 07960
Under License From:
Laboratoire HRA Pharma
92330 Chatillon, France
Product of Spain
Manufactured By:
Delpharm Lille S.A.S.
PARC D'ACTIVITE ROUBAIX EST
22 RUE DE TOUFFLERS
CS 50070
59492 LYS LEZ LANNOY
FRANCE
5044762

ella®
ulipristal acetate table 30 mg
N 73302-456-1
Push through from front
Contains 1
30 mg tablet
Manufactured for:
HRA Pharma America Inc.,
36 Cattano Ave. Suite 400
Morristown, NJ 07960
LOT:
EXP:
5044761